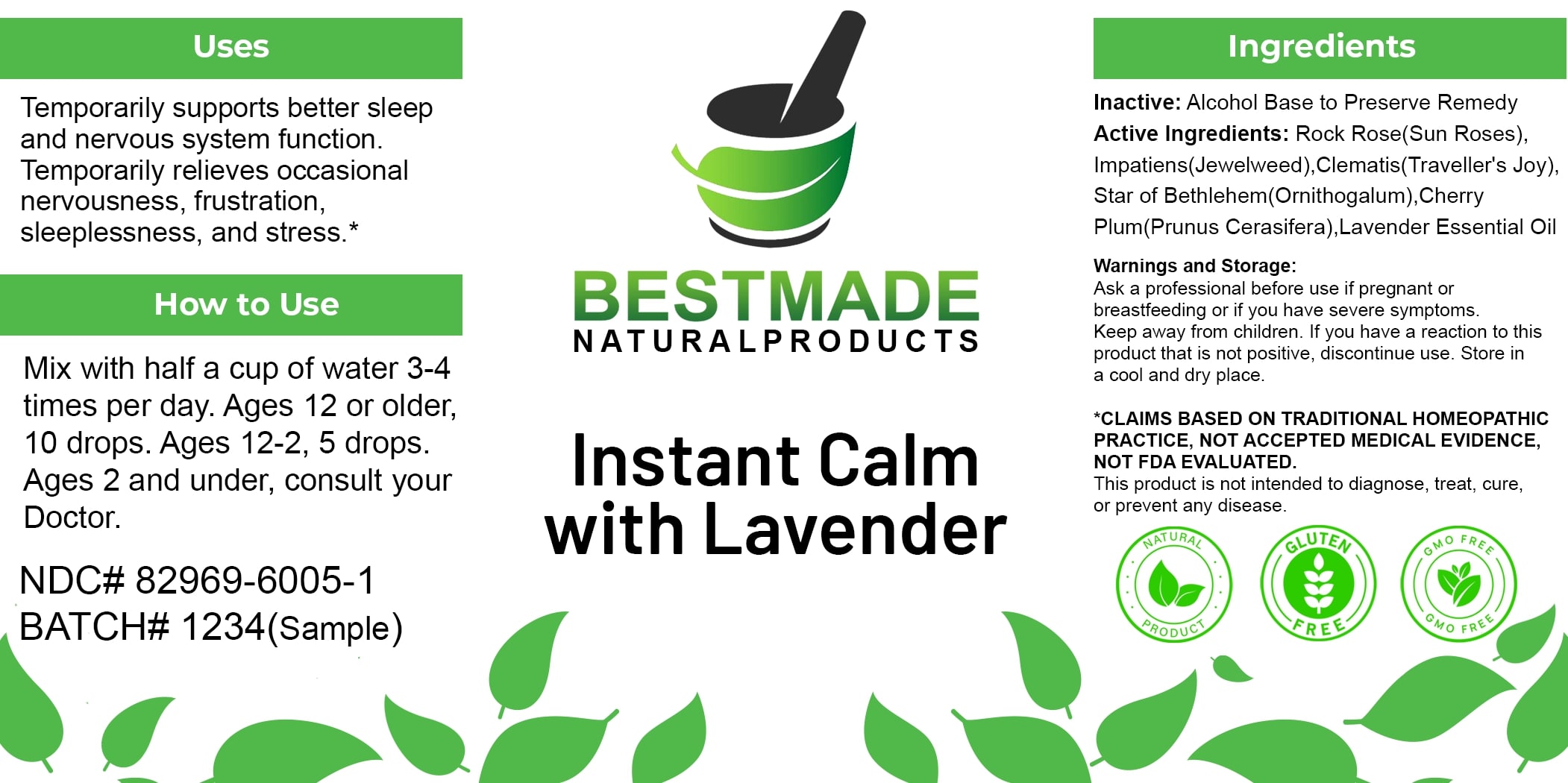 DRUG LABEL: Bestmade Natural Products Instant Calm with Lavender
NDC: 82969-6005 | Form: LIQUID
Manufacturer: Bestmade Natural Products
Category: homeopathic | Type: HUMAN OTC DRUG LABEL
Date: 20250314

ACTIVE INGREDIENTS: IMPATIENS GLANDULIFERA FLOWER 6 [hp_X]/6 [hp_X]; CLEMATIS VITALBA FLOWER 6 [hp_X]/6 [hp_X]; ORNITHOGALUM UMBELLATUM FLOWERING TOP 6 [hp_X]/6 [hp_X]; HELIANTHEMUM NUMMULARIUM FLOWER 6 [hp_X]/6 [hp_X]; PRUNUS CERASIFERA FLOWER 6 [hp_X]/6 [hp_X]
INACTIVE INGREDIENTS: ALCOHOL 6 [hp_X]/6 [hp_X]

Instant Calm with Lavender

DOSAGE AND ADMINISTRATION

How to Use

Mix with half a cup of water 3-4 times per day. Ages 12 or older, 10 drops. Ages 12-2, 5 drops. Ages 2 and under, consult your Doctor.

Inactive:

Alcohol Base to Preserve Product

Active Ingredients:
Rock Rose (Sun Roses), Impatiens (Jewelweed), Clematis(Traveller's Joy), Star of Bethlehem (Ornithogalum), Cherry Plum(Prunus Cerasifera), Lavender Essential Oil

Uses

Temporarily supports better sleep and nervous system function. Temporarily relieves occasional nervousness, frustration, sleeplessness, and stress.*

*CLAIMS BASED ON TRADITIONAL HOMEOPATHIC PRACTICE, NOT ACCEPTED MEDICAL EVIDENCE, NOT FDA EVALUATED.

This product is not intended to diagnose, treat, cure, or prevent any disease.

Uses

Temporarily supports better sleep and nervous system function. Temporarily relieves occasional nervousness, frustration, sleeplessness, and stress.*

*CLAIMS BASED ON TRADITIONAL HOMEOPATHIC PRACTICE, NOT ACCEPTED MEDICAL EVIDENCE, NOT FDA EVALUATED.

This product is not intended to diagnose, treat, cure, or prevent any disease.

KEEP OUT OF REACH OF CHILDREN

Warnings and Storage:

Ask a professional before use if pregnant or breastfeeding or if you have severe symptoms. Keep away from children. If you have a reaction to this product that is not positive, discontinue use. Store in a cool and dry place.

Warnings and Storage:

Ask a professional before use if pregnant or breastfeeding or if you have severe symptoms. Keep away from children. If you have a reaction to this product that is not positive, discontinue use. Store in a cool and dry place.

*CLAIMS BASED ON TRADITIONAL HOMEOPATHIC PRACTICE, NOT ACCEPTED MEDICAL EVIDENCE NOT FDA EVALUATED.

This product is not intended to diagnose, treat, cure, or prevent any disease.

Entire package label